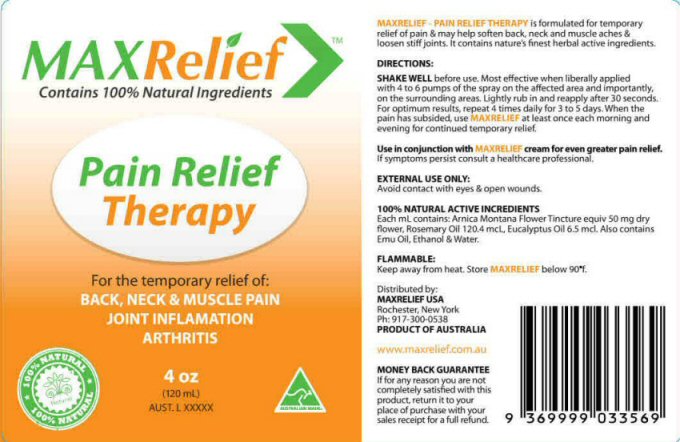 DRUG LABEL: MAXRELIEF
NDC: 76509-001 | Form: SPRAY
Manufacturer: Natures Investment Holdings Pty Ltd
Category: homeopathic | Type: HUMAN OTC DRUG LABEL
Date: 20111219

ACTIVE INGREDIENTS: ARNICA MONTANA FLOWER 50 mg/120 mL; ROSEMARY OIL 110 mg/120 mL; EUCALYPTUS OIL 6 mg/120 mL
INACTIVE INGREDIENTS: EMU OIL; ALCOHOL; WATER

Active Ingredient Section

100% NATURAL ACTIVE INGREDIENTS

Each ml contains: Arnica Montana Flower Tincture equiv 50 mg dry flower, Rosemary Oil 120.4 mcl, Eucalyptus Oil 6.5 mcl

Purpose Section

MAXRELIEF PAIN RELIEF THERAPY is formulated for temporary relief of pain and may help soften back, neck, and muscle aches and loosen stiff joints. It contains nature's finest herbal active ingredients.

Keep Out of Reach of Children Section

Enter section text here

Indications & Usage Section

Pain Relief Therapy For the temporary relief of: BACK, NECK, and MUSCLE PAIN JOINT INFLAMMATION ARTHRITIS

Warnings Section

EXTERNAL USE ONLY: Avoid contact with eyes and open wounds.

FLAMMABLE: Keep away from heat. Store MAXRELIEF below 90 degrees F

Directions Section

DIRECTIONS:

SHAKE WELL before using. Most effective when liberally applied with 4 to 6 pumps of the spray on the affected area and importantly, on the surrounding area. Lightly rub in and reapply after 30 seconds. For optimum results, repeat 4 times daily for 3 to 5 days. When the pain has subsided, use MAXRELIEF at least once each morning and evening for continued temporary relief.

Use in conjunction with MAXRELIEF cream for even greater pain relief. If symptoms persist consult a healthcare professional.

Inactive Ingredient Section

Also contains Emu Oil, Ethanol and Water.

Money Back Guarantee Section

MONEY BACK GUARANTEE

If for any reason you are not completely satisfied with this product, return it to your place of purchase with your sales receipt for a full refund.

Label Information Section

MAXRelief tm Contains 100% Natural Ingredients 100% NATURAL AUSTRALIAN MADE 4 oz (120 ml) AUST. L XXXXX

Distributed by: MAXRELIEF USA Rochester, New York ph: 917-300-0538

PRODUCT OF AUSTRALIA www.maxrelief.com.au